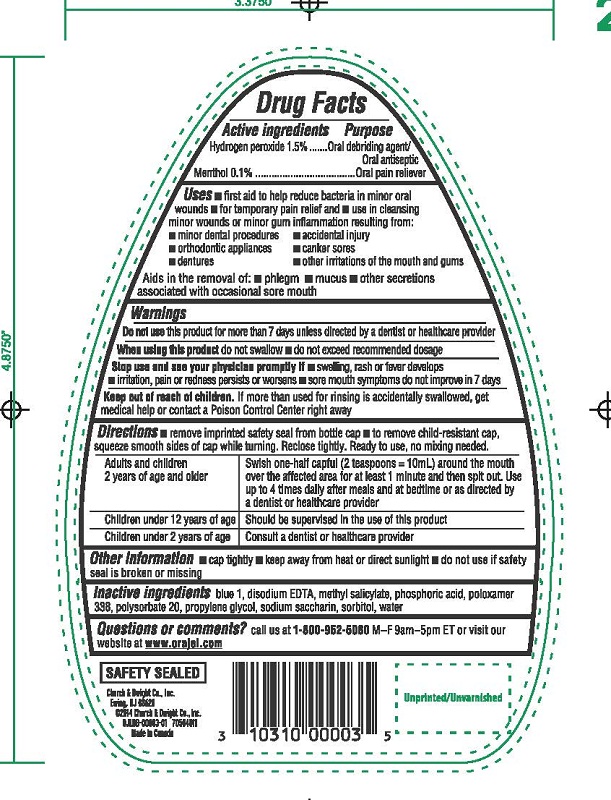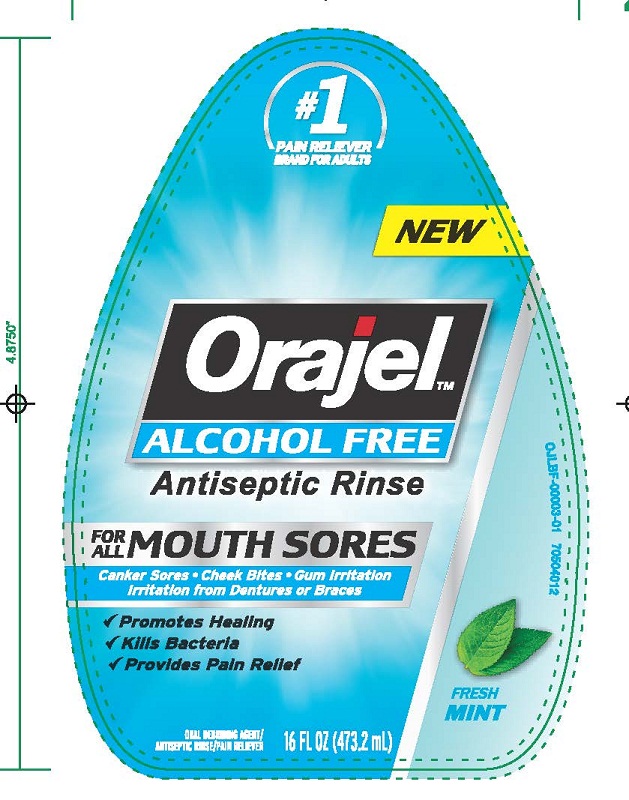 DRUG LABEL: Orajel Alcohol Free Antiseptic Rinse
NDC: 62864-759 | Form: LIQUID
Manufacturer: Church & Dwight Canada Corp
Category: otc | Type: HUMAN OTC DRUG LABEL
Date: 20141023

ACTIVE INGREDIENTS: HYDROGEN PEROXIDE 1.5 mL/1 mL; MENTHOL 1 mg/1 mL
INACTIVE INGREDIENTS: FD&C BLUE NO. 1; EDETATE DISODIUM; METHYL SALICYLATE; PHOSPHORIC ACID; POLOXAMER 338; POLYSORBATE 20; PROPYLENE GLYCOL; SACCHARIN SODIUM; SORBITOL; WATER

DRUG FACTS Orajel Alcohol Free Antiseptic Rinse

Active ingredient

Hydrogen peroxide 1.5%

Menthol 0.1%

Purpose

Oral debriding agent/Oral antiseptic

Oral pain reliever

Uses

- first aid to help reduce bacteria in minor oral wounds
- for temporary pain relief and
- use in cleansing minor wounds or minor gum inflammation resulting from:
- minor dental procedures
- accidental injury
- orthodontic appliances
- canker sores
- dentures
- other irritations of the mouth and gums

Aids in the removal of

- phlegm
- mucus
- other secretions associated with occasional sore mouth

Warnings

Do not use this product for more than 7 days unless directed by a dentist or healthcare provider

When using this product

- do not swallow
- do not exceed recommended dosage

Stop Use and see your physician promptly if

- swelling, rash or fever develops
- irritations, pain or redness persists or worsens
- sore mouth symptoms do not improve in 7 days

Keep out of reach of children. If more than used for rinsing is accidentally swallowed, get medical help or contact a poison Control Center right away

Directions

- remove imprinted safety seal from bottle cap
- to remove child-resistant cap, squeeze smooth sides of cap while turning. Reclose tightly. Ready to use, no mixing needed.

Adults and children; 2 years of age and older |  |  | Swish one-half capful (2 tesapoons=10mL) around the mouth over the affected area for at least 1 minute and then spit out. Use up to 4 times daily after meals and at bedtime or as directed by a dentist or healthcare provider
Children under 12 years of age |  |  | Should be supervised in the use of this product
Children under 2 years of age |  |  | Consult a dentist or healthcare provider

Other Information

- cap tightly
- keep away from heat or direct sunlight
- do not use if safety seal is broken or missing

INACTIVE INGREDIENT

Inactive ingredients blue 1, disodium EDTA, methyl salicylate, phosphoric acid, poloxamer 338, polysorbate 20, propylene glycol, sodium saccharin, sorbitol, water

Orajel Alcohol Free Antiseptic Rinse

#1

PAIN RELIEVER

BRAND FOR ADULTS

NEW

Orajel

ALCOHOL FREE Antiseptic rinse

FOR ALL MOUTH SORES

Canker Sores Cheek Bites Gum Irritation

Irritatrion from Dentures or Braces

Promotes Healing

Kills Bacteria

Provides Pain Relief

FRESH MINT

ORAL DEBRIDING AGENT / ANTISEPTIC RINSE / PAIN RELIEVER

16 FL OZ (473.2 mL)

Front Label OJLBF-00003-01.jpg

Back Label OJLBB-00003-01.jpg

Questions or comments call us at 1–800–952–5080 M–F 9am–5pm ET or visit our website atwww.orajel.com